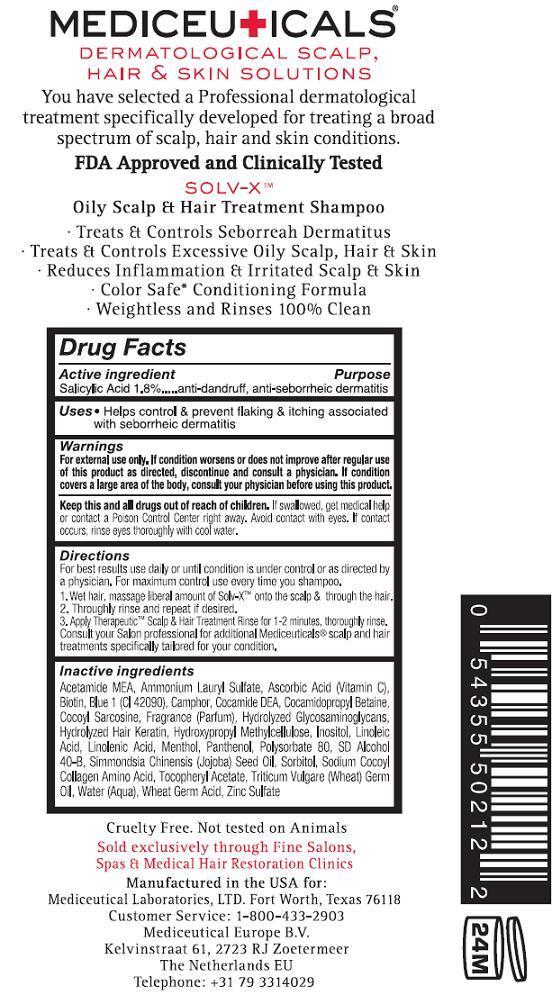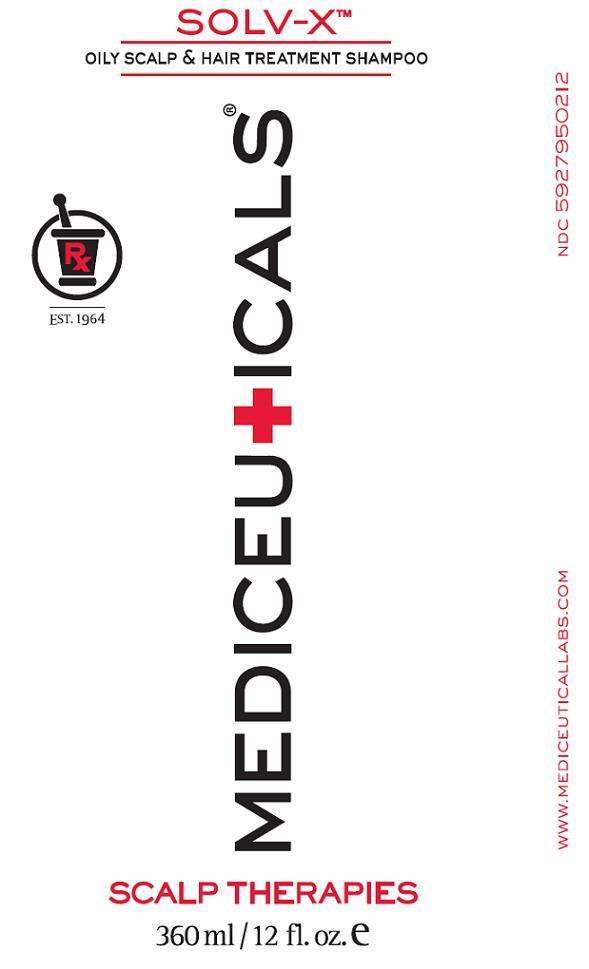 DRUG LABEL: SOLV X
NDC: 59279-502 | Form: SHAMPOO
Manufacturer: Mediceutical Laboratories, LTD
Category: otc | Type: HUMAN OTC DRUG LABEL
Date: 20121001

ACTIVE INGREDIENTS: SALICYLIC ACID 18 mg/1 L
INACTIVE INGREDIENTS: ACETIC MONOETHANOLAMIDE; AMMONIUM LAURYL SULFATE; ASCORBIC ACID; BIOTIN; FD&C BLUE NO. 1; CAMPHOR (SYNTHETIC); COCO DIETHANOLAMIDE; COCAMIDOPROPYL BETAINE; SARCOSINE; HYPROMELLOSES; INOSITOL; LINOLEIC ACID; LINOLENIC ACID; MENTHOL; PANTHENOL; POLYSORBATE 80; ALCOHOL; JOJOBA OIL; SORBITOL; .ALPHA.-TOCOPHEROL ACETATE, D-; WHEAT GERM OIL; WATER; ZINC SULFATE

SOLV-X

Active ingredient

Salicylic Acid 1.8%

Purpose

anti-dandruff, anti-seborrheic, dermatitis

Uses

- Helps control and prevent flaking and itching associated with seborrheic dermatitis

Warnings

For external use only. If condition worsens or does not improve after regular use of this product as directed, discontinue and consult a physician. If condition covers a large area of the body, consult your physician before using this product.

Keep this and all drugs out of reach of children.

If swallowed, get medical help or contact a Poison Control Center right away. Avoid contact with eyes. If contact occurs, rinse eyes thoroughly with cool water.

Directions

For best results use daily or until condition is under control or as directed by a physician.

For maximum control use every time you shampoo.

1. Wet hair, massage liberal amount of Solv-XTM onto the scalp and through the hair
2. Thoroughly rinse and repeat if desired
3. Apply TherapeuticTM Scalp and Hair Treatment Rinse for 1-2 minutes, thoroughly rinse.

Consult your Salon professional for additional Mediceuticals® scalp and hair treatments specifically tailored for your condition.

Inactive ingredients

Acetamide MEA, Ammonium Lauryl Sulfate, Ascorbic Acid (Vitamin C), Biotin, Blue 1 (Cl 42090), Camphor, Cocamide DEA, Cocamidopropyl Betaine, Cocoyl Sarcosine, Fragrance (Parfum), Hydrolyzed Glycosaminoglycans, Hydrolyzed Hair Keratin, Hydroxypropyl Methylcellulose, Inositol, Linoleic Acid, Linolenic Acid, Menthol, Panthenol, Polysorbate 80, SD Alcohol 40-B, Simmondsia Chinesis (Jojoba) Seed Oil, Sorbitol, Sodium Cocoyl Collagen Amino Acid, Tocopheryl Acetate, Triticum Vulgare (Wheat) Germ Oil, Water (Aqua), Wheat Germ Acid, Zinc Sulfate

Package Label-Principal Display Panel

SOLV-XTM

OILY SCALP AND HAIR TREATMENT SHAMPOO

MEDICEUTICALS®
Cruelty Free. Not tested on Animals.
Sold exclusively through fine Salons, Spas and Hair Restoration Clinics

Manufactured in the USA for:

Mediceutical Laboratories, LTD Fort Worth, Texas 76118
Customer Service: 1-800-433-2903

Mediceutical Europe B.V.

Kelvinstraat 61,2723 RJ Zoetermeer The Netherlands EU

Telephone: +31 79 3314029

NDC 5927950233 SOLV-X 33.8 fl oz

NDC 5927950206 SOLV-X 6 fl oz

NDC 5927950212 SOLV-X 12 fl oz

Front

Back